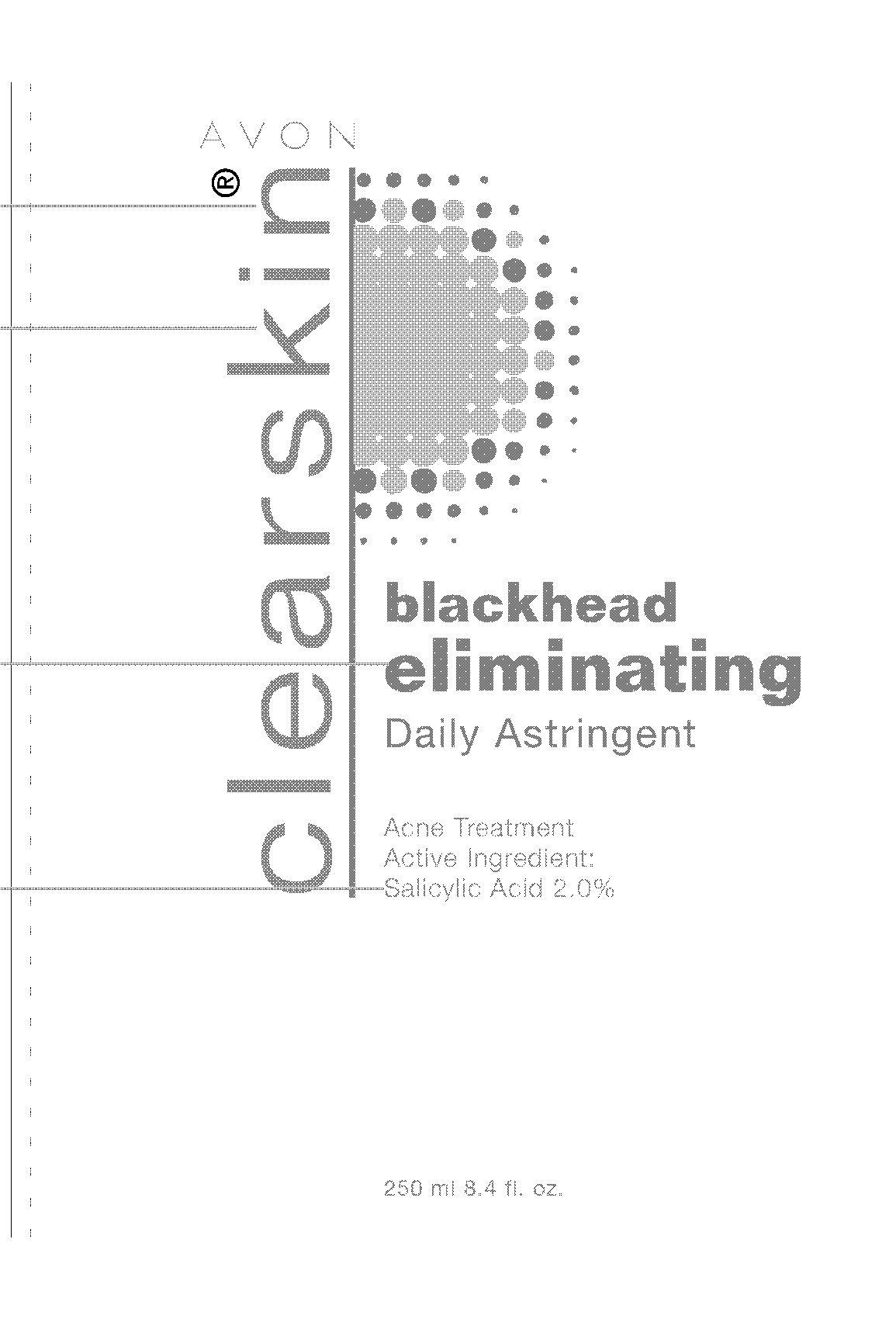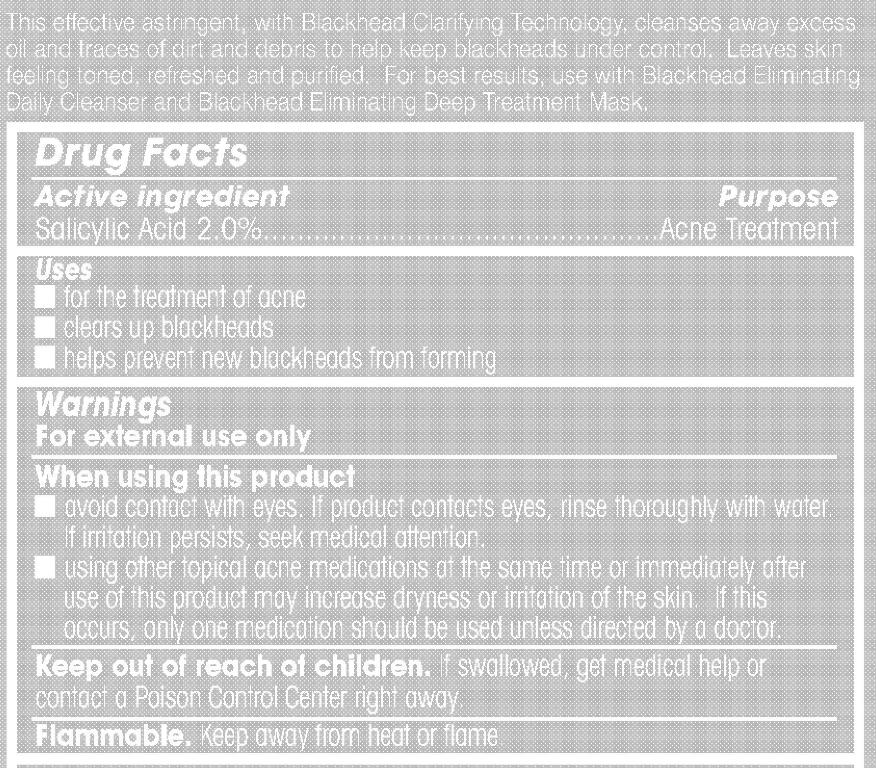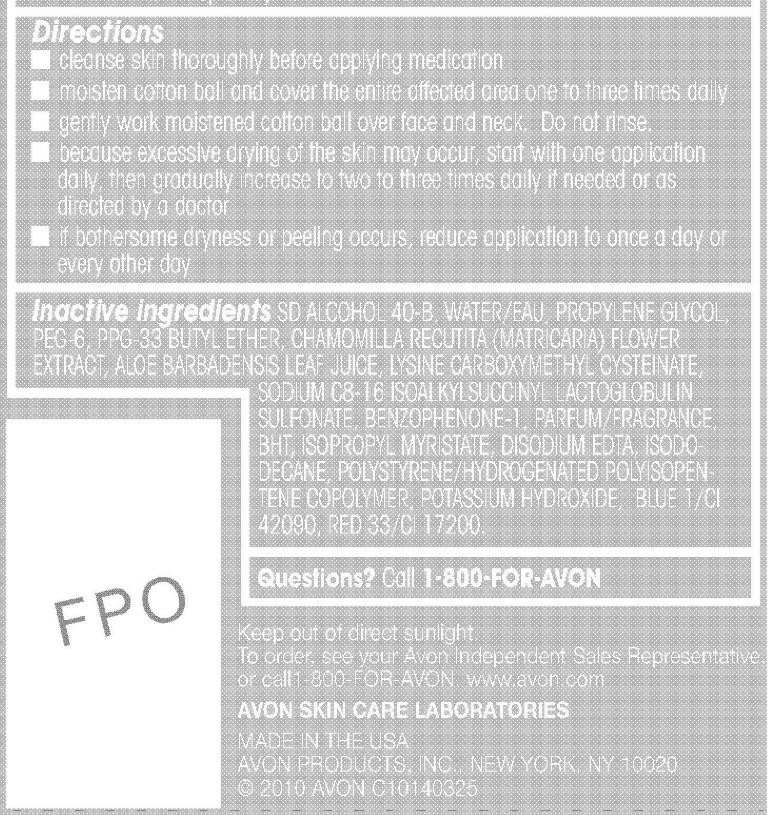 DRUG LABEL: Clearskin
NDC: 10096-0183 | Form: LIQUID
Manufacturer: Avon Products, Inc.
Category: otc | Type: HUMAN OTC DRUG LABEL
Date: 20091216

ACTIVE INGREDIENTS: Salicylic Acid 5 mL/250 mL
INACTIVE INGREDIENTS: WATER; PROPYLENE GLYCOL; ISOPROPYL MYRISTATE; ISODODECANE; POTASSIUM HYDROXIDE

Drug Facts

Active ingredient Purpose

Salicylic Acid 2.0%...............................................Acne Treatment

Uses

- for the treatment of acne
- clears up blackheads
- helps prevent new blackheads from forming

Warnings
For external use only

When using this product

- avoid contact with eyes. If product contacts eyes, rinse thoroughly with water. If irritation persists, seek medical attention.
- using other topical acne medications at the same time or immediately after use of this product may increase dryness or irritation of the skin. If this occurs, only one medication should be used unless directed by a doctor.

Keep out of reach of children. If swallowed, get medical help or
contact a Poison Control Center right away.

GENERAL PRECAUTIONS

Flammable. Keep away from heat or flame.

Directions

- cleanse skin thoroughly before applying medication
- moisten cotton ball and cover the entire affected area one to three times daily
- gently work moistened cotton ball over face and neck. Do not rinse.
- because excessive drying of the skin may occur, start with one application daily, then gradually increase to two to three times daily if needed or as directed by a doctor
- if bothersome dryness or peeling occurs, reduce application to once a day or every other day

INACTIVE INGREDIENT

Inactive ingredients SD ALCOHOL 40-B, WATER/EAU, PROPYLENE GLYCOL,
PEG-6, PPG-33 BUTYL ETHER, CHAMOMILLA RECUTITA (MATRICARIA) FLOWER
EXTRACT, ALOE BARBADENSIS LEAF JUICE, LYSINE CARBOXYMETHYL CYSTEINATE,
SODIUM C8-16 ISOALKYLSUCCINYL LACTOGLOBULIN
SULFONATE, BENZOPHENONE-1, PARFUM/FRAGRANCE,
BHT, ISOPROPYL MYRISTATE, DISODIUM EDTA, ISODODECANE,
POLYSTYRENE/HYDROGENATED POLYISOPENTENE
COPOLYMER, POTASSIUM HYDROXIDE, BLUE 1/CI
42090, RED 33/CI 17200.

Questions? Call 1-800-FOR-AVON

STORAGE AND HANDLING

Keep out of direct sunlight.